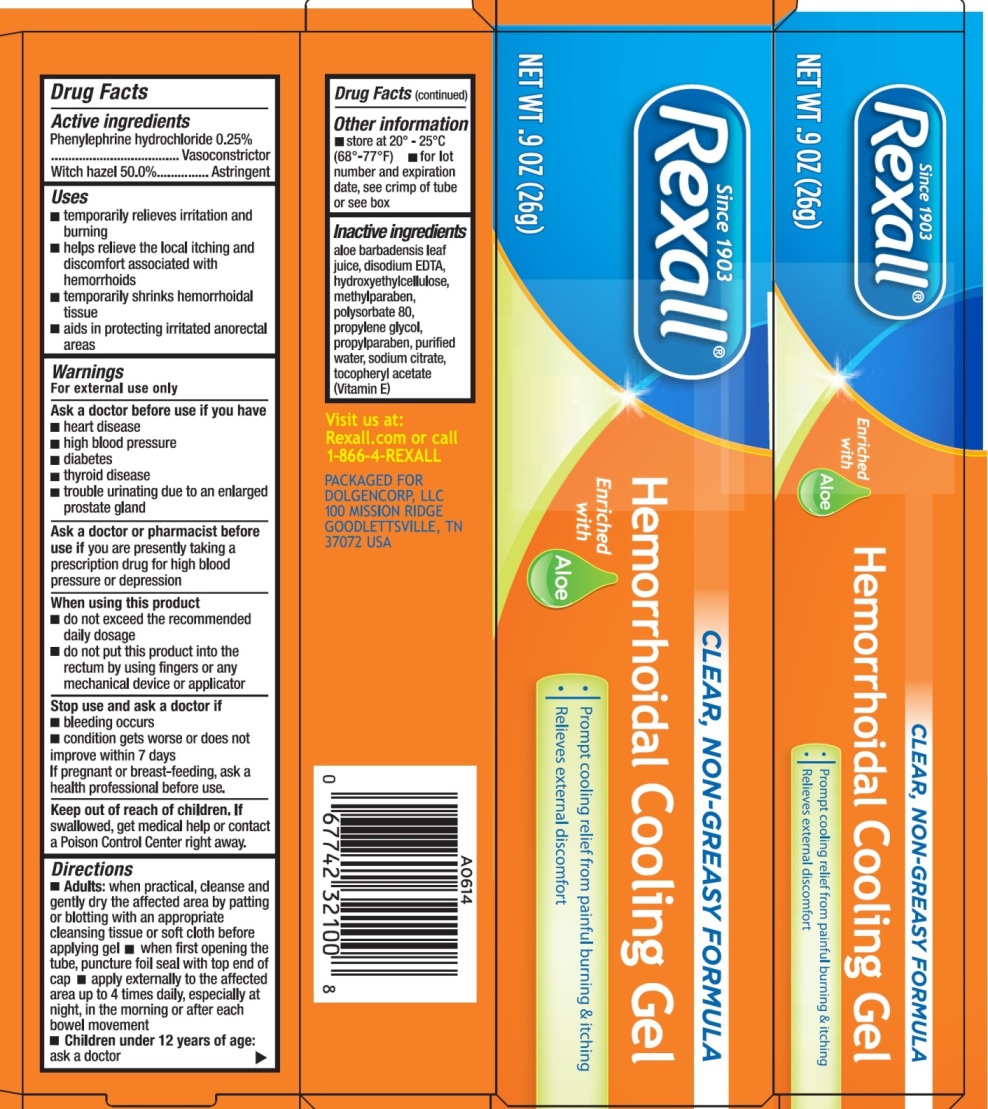 DRUG LABEL: REXALL HEMORRHOIDAL COOLING
NDC: 55910-416 | Form: GEL
Manufacturer: Dolgencorp, Inc.
Category: otc | Type: HUMAN OTC DRUG LABEL
Date: 20170713

ACTIVE INGREDIENTS: PHENYLEPHRINE HYDROCHLORIDE 0.25 g/100 g; WITCH HAZEL 50 g/100 g
INACTIVE INGREDIENTS: ALOE VERA LEAF; EDETATE DISODIUM; METHYLPARABEN; POLYSORBATE 80; PROPYLENE GLYCOL; PROPYLPARABEN; WATER; SODIUM CITRATE; .ALPHA.-TOCOPHEROL

REXALL HEMORRHOIDAL COOLING GEL

Active Ingredients

Phenylephrine Hydrochloride 0.25%
Witch Hazel 50%

Purpose

Vasoconstrictor
Astringent

Uses

- temporary relieves irritation and burning
- helps relieve the local itching and discomfort associated with hemorrhoids
- temporarily shrinks hemorrhoidal tissue
- aids in protecting irritated anorectal areas

Warnings

For external use only

Ask a doctor before use if you have

- heart disease
- high blood pressure
- diabetes
- thyroid disease
- trouble urinating due to an enlarged prostate gland

Ask a doctor or pharmacist before use if you are presently taking a prescription drug for high blood pressure or depression.

When using this product

- do not exceed the recommended daily dosage
- do not put this product into the rectum by using fingers or any mechanical device or applicator

Stop use and ask a doctor if

- bleeding occurs
- condition gets worse or does not improve within 7 days

If pregnant or breast-feeding, ask a health professional before use.

Keep out of reach of children

If swallowed, get medical help or contact a Poison Control Center right away.

Directions

- Adults: when practical, cleanse and gently dry the affected area by patting or blotting with an appropriate cleansing tissue or soft cloth before applying gel
- when first opening the tube, puncture foil seal with top end of cap
- apply externally to the affected area up to 4 times daily, especially at night, in the morning or after each bowel movement
- Children under 12 years of age: ask a doctor

Other information

- store at 20°-25°C (68°-77°F)
- for lot number and expiration date, see crimp of tube or see box

Inactive ingredients

aloe barbadensis leaf juice, disodium EDTA, hydroxyethylcellulose, methylparaben, polysorbate 80, propylene glycol, propylparaben, purified water, sodium citrate, tocopheryl acetate (Vitamin E)

Principal display panel - 26 g Carton Label

REXALL HEMORRHOIDAL COOLING GEL

NET WT .9 OZ (26 g)